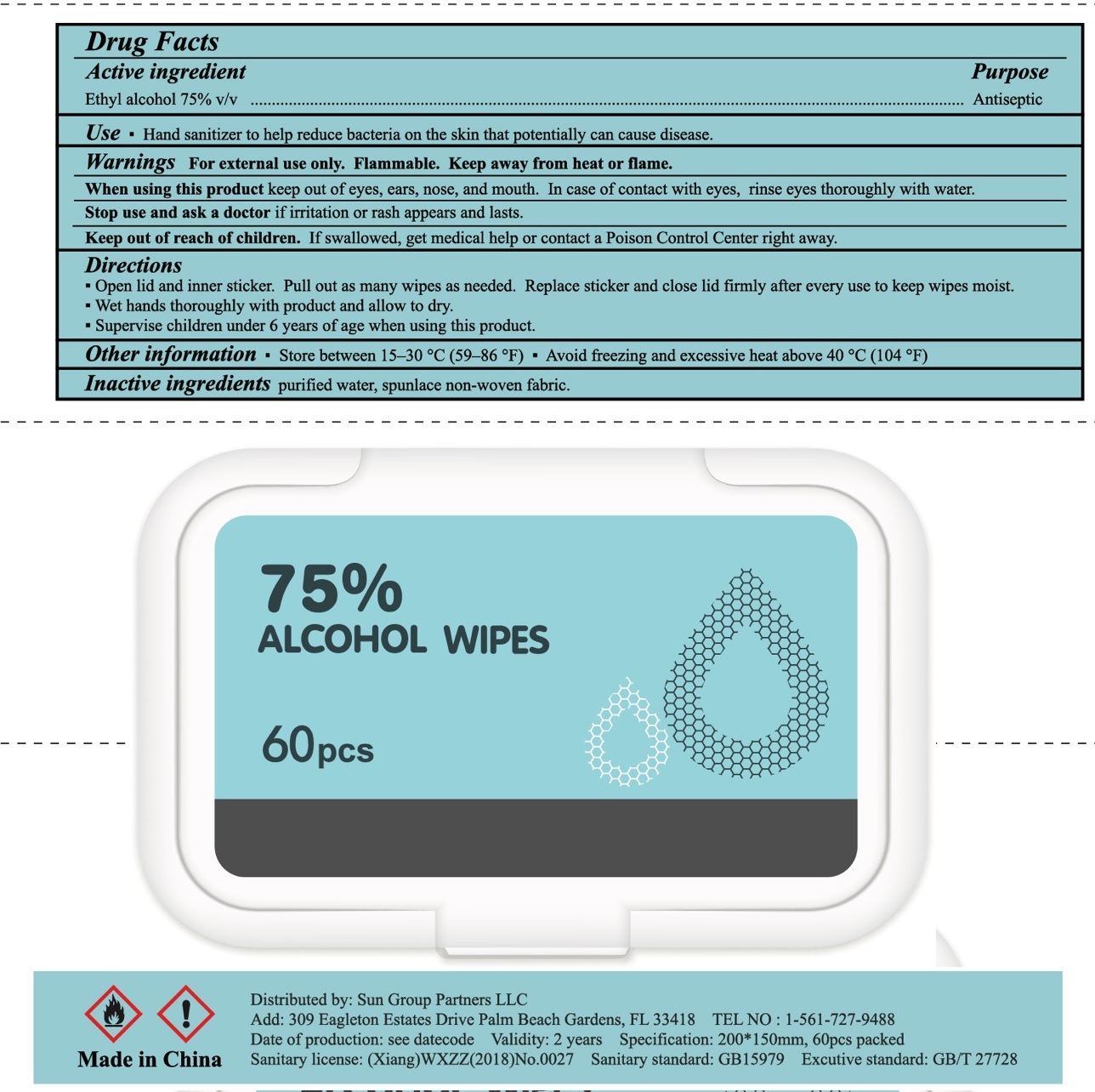 DRUG LABEL: Alcohol Wipes
NDC: 78724-006 | Form: SWAB
Manufacturer: Jiebao Daily Chemical (Xiangxi)Co.,Ltd
Category: otc | Type: HUMAN OTC DRUG LABEL
Date: 20200810

ACTIVE INGREDIENTS: ALCOHOL 75 g/100 g
INACTIVE INGREDIENTS: water; BENZALKONIUM CHLORIDE

alcohol Wipes

Active Ingredient

Ethyl Alcohol 75% v/v

Purpose

Antiseptic

USE

- Hand sanitizer to help reduce bacteria on the skin that potentially can cause disease.

Warning

- Flammable, keep away from heat or flame.
- For external use only.
- When using this product, keep out of eyes, ears, nose and mouth. In case of contact, rinse eyes thoroughly with water
- Stop use and ask a doctor if irritatio or rash appears and lasts.

Other information:

- Store between 15-30℃ (59-86℉)
- avoid freezing and excessive heat above 40℃ (104℉)

KEEP OUT OF REACH OF CHILDREN

●If swallowed, get medical help or contact a Poison Contrl Center right away.

Directions

- Open lid and inner sticker. Pull out as many wipes as needed. Replace sticker and close lid firmly after every use to keep wipes moist.
- wet hands thoroughly with product and allow to dry.
- supervise under 6 years of age when using this product.

Inactive ingredients

purified water, sunlace non-woven fabric.